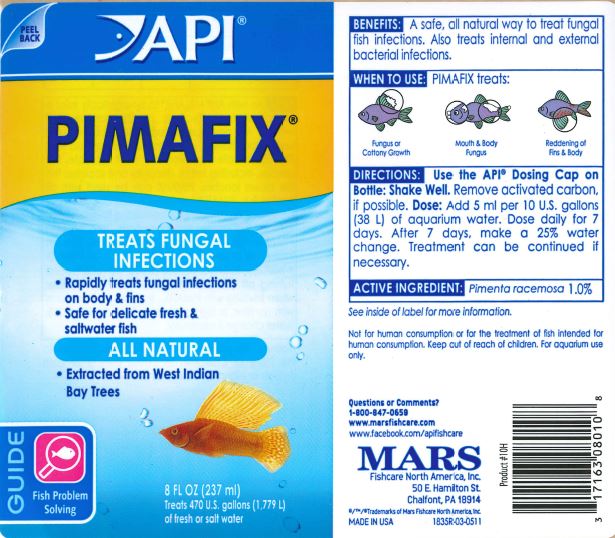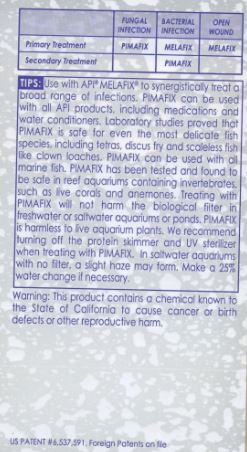 DRUG LABEL: API PIMAFIX
                        
NDC: 17163-010 | Form: LIQUID
Manufacturer: MARS FISHCARE NORTH AMERICA, INC.
Category: animal | Type: OTC ANIMAL DRUG LABEL
Date: 20191219

ACTIVE INGREDIENTS: BAY OIL (PIMENTA RACEMOSA) 1 g/100 mL

Drug Label

DESCRIPTION

BENEFITS:

A safe, all natural way to treat fungal fish infections.

Also treats internal and external bacterial infections.

INDICATIONS AND USAGE

WHEN TO USE:

PIMAFIX treats:

Fungus or Cottony Growth

Mouth and Body Fungus

Reddening of Fins and Body

DIRECTIONS:

Use the API Dosing Cap on the Bottle:

Shake Well. Remove activated carbon, if possible.

Dose:

Add 5 ml per 10 U.S. gallons (38 L) of aquarium water.

Dose daily after 7 days. After 7 days, make a 25% water change. Treatment can be continued if necessary.

ACTIVE INGREDIENT: Pimenta racemosa 1.0%

See inside of label for more information.

USER SAFETY WARNINGS

FUNGAL INFECTION BACTERIAL INFECTION OPEN WOUND

Primary Treatment PIMAFIX MELAFIX MELAFIX

Secondary Treatment PIMAFIX

TIPS:

Use with API MELAFIX to synergistically treat a broad range of infections. PIMAFIX can be used with all API products, including medications and water conditioners. Laboratory studies proved that PIMAFIX is safe for even the most delicate fish species, including tetras, discus fry and scaleless fish like clown loaches. PIMAFIX can be used with all marine fish. PIMAFIX has been tested and found to be safe in reef aquariums containing invertebrates, such as live corals and anemones. Treating with PIMAFIX will not harm the biological filter in freshwater or saltwater aquariums or ponds. PIMAFIX is harmless to live aquarium plants. We recommend turning off the protein skimmer and UV sterilizer when treating with PIMAFIX. In saltwater aquariums with no filter, a slight haze may form. Make a 25% water change if necessary.

Warning:

This product contains a chemical known to the State of California to cause cancer or birth defects or other reproductive harm. Not for human consumption or for the treatment of fish intended for human consumption. Keep out of reach of children. For aquarium use only.

Questions or Comments?

1-800-847-0659

www.marsfishcare.com

WWW.facebook.com/apifishcare

PACKAGE LABEL

API

PIMAFIX

TREATS FUNGAL

INFECTIONS

Rapidly treats fungal infections

on body and fins

Safe for delicate fresh and

saltwater fish

ALL NATURAL

Extracted from West Indian

Bay Trees

GUIDE

Fish Problem

Solving

8 FL OZ (237 mL)

Treats 470 U.S. gallons (1,779) L)

of fresh or salt water